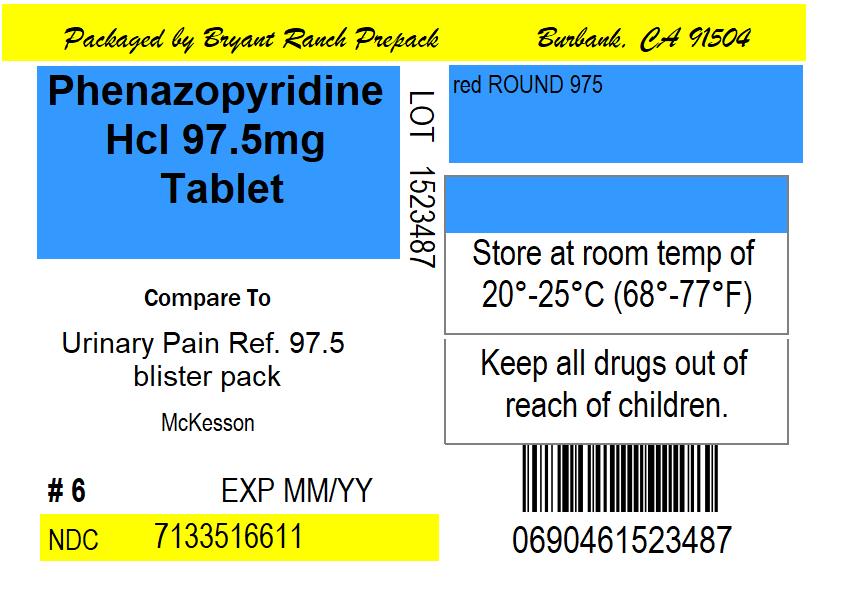 DRUG LABEL: Sunmark Urinary Pain Relief Maximum Strength
                        
NDC: 71335-1661 | Form: TABLET
Manufacturer: Bryant Ranch Prepack
Category: otc | Type: HUMAN OTC DRUG LABEL
Date: 20211228

ACTIVE INGREDIENTS: PHENAZOPYRIDINE HYDROCHLORIDE 97.5 mg/1 1
INACTIVE INGREDIENTS: LACTOSE, UNSPECIFIED FORM; MAGNESIUM SILICATE; MAGNESIUM STEARATE

Drug Facts

ACTIVE INGREDIENT

PHENAZOPYRIDINE HYDROCHLORIDE 97.5 MG

PURPOSE

PHENAZOPYRIDINE HYDROCHLORIDE URINARY ANALGESIC

WARNINGS

DO NOT EXCEED RECOMMENDED DOSAGE

ASK DOCTOR

ASK DOCTOR BEFORE USE
IF YOU HAVE KIDNEY DISEASE
ALLERGIES TO FOODS,PRESERVATIVES OR DYES
HAD A HYPERSENSITIVE REACTION TO PHENAZOPYRIDINE

WHEN USING

WHEN USING THIS PRODUCT
STOMACH UPSET MAY OCCUR,TAKING THIS PRODUCT WITH OR AFTER MEALS MAY REDUCE STOMACH UPSET
YOUR URINE WILL BECOME REDDISH ORANGE IN COLOR.THIS IS NOT HARMFUL,BUT CARE SHOULD BE TAKEN TO
AVOID STAINING CLOTHING OR OTHER ITEMS.

STOP USE

STOP USE AND ASK A DOCTOR
IF YOUR SYMPTOMS LAST FOR MORE THAN 2 DAYS
YOU SUSPECT YOU ARE HAVING AN ADVERSE REACTION TO THE MEDICATION

PREGNANCY OR BREAST FEEDING

ASK A HEALTH PROFESSIONAL BEFORE US

KEEP OUT OF REACH OF CHILDREN

IN CASE OF OVERDOSE ,GET MEDICAL HELP OR CONTACT A POISON CONTROL CENTER RIGHT AWAY.

INDICATIONS & USAGE

Use; fast relief from urinary pain,burning,urgency and frequency associated with urinary tract infections.

INACTIVE INGREDIENT

Lactose, magnesium silicate, magnesium stearate, microcrystalline cellulose,
pharmaceutical glaze, and sodium starch glycolate.

DOSAGE & ADMINISTRATION

Adults and Children 12 years of age and over; take 2 tablets 3 times daily with a full glass of water,with or after meals as needed.
Children under 12 years of age; consult a doctor.
Do not use for more than 2 days (12 tablets) without consulting a Doctor.

HOW SUPPLIED

NDC: 71335-1661-1: 6 Tablets in a BOTTLE

NDC: 71335-1661-2: 12 Tablets in a BOTTLE

NDC: 71335-1661-3: 36 Tablets in a BOTTLE

NDC: 71335-1661-4: 20 Tablets in a BOTTLE

NDC: 71335-1661-5: 10 Tablets in a BOTTLE

PACKAGE LABEL

Phenazopyridine Hcl 97.5mg Tablet